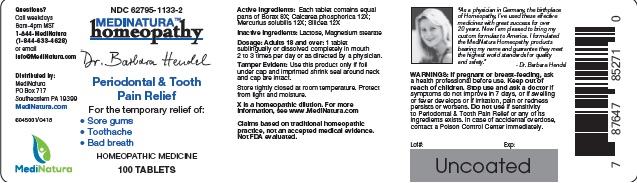 DRUG LABEL: Hendel Periodontal and Tooth Pain Relief
NDC: 62795-1133 | Form: TABLET
Manufacturer: MediNatura Inc
Category: homeopathic | Type: HUMAN OTC DRUG LABEL
Date: 20220822

ACTIVE INGREDIENTS: SODIUM BORATE 8 [hp_X]/1 1; TRIBASIC CALCIUM PHOSPHATE 12 [hp_X]/1 1; MERCURIUS SOLUBILIS 12 [hp_X]/1 1; SILICON DIOXIDE 12 [hp_X]/1 1
INACTIVE INGREDIENTS: LACTOSE MONOHYDRATE; MAGNESIUM STEARATE

Hendel Periodontal and Tooth Pain Relief

WARNINGS

WARNINGS: If pregnant or breast-feeding, ask a health professional before use. Keep out of reach of children. Stop use and ask doctor if symptoms do not improve in 7 days or if swelling or fever develops or if irritation, pain or redness persist or worsens.

Do not use if sensitivity to Periodontal & Tooth Pain Relief or any of its ingredients exists. In case of accidental overdose, contact a Poison Control Center immediately.

PURPOSE

Periodontal & Tooth Pain Relief

KEEP OUT OF REACH OF CHILDREN

USES

For the temporary relief of:

• Sore gums
• Toothache
• Bad breath

ACTIVE INGREDIENTS

Each tablet contains equal parts of Borax 8X; Calcarea phosphorica 12X; Mercurius solubilis 12X; Silicea 12X

INACTIVE INGREDIENTS

Lactose, Magnesium stearate

DIRECTIONS

Dosage: Adults 18 and over: 1 tablet sublingually or dissolved completely in mouth 2 to 3 times per day or as directed by a physician.

PACKAGE LABEL

Add image transcription here...